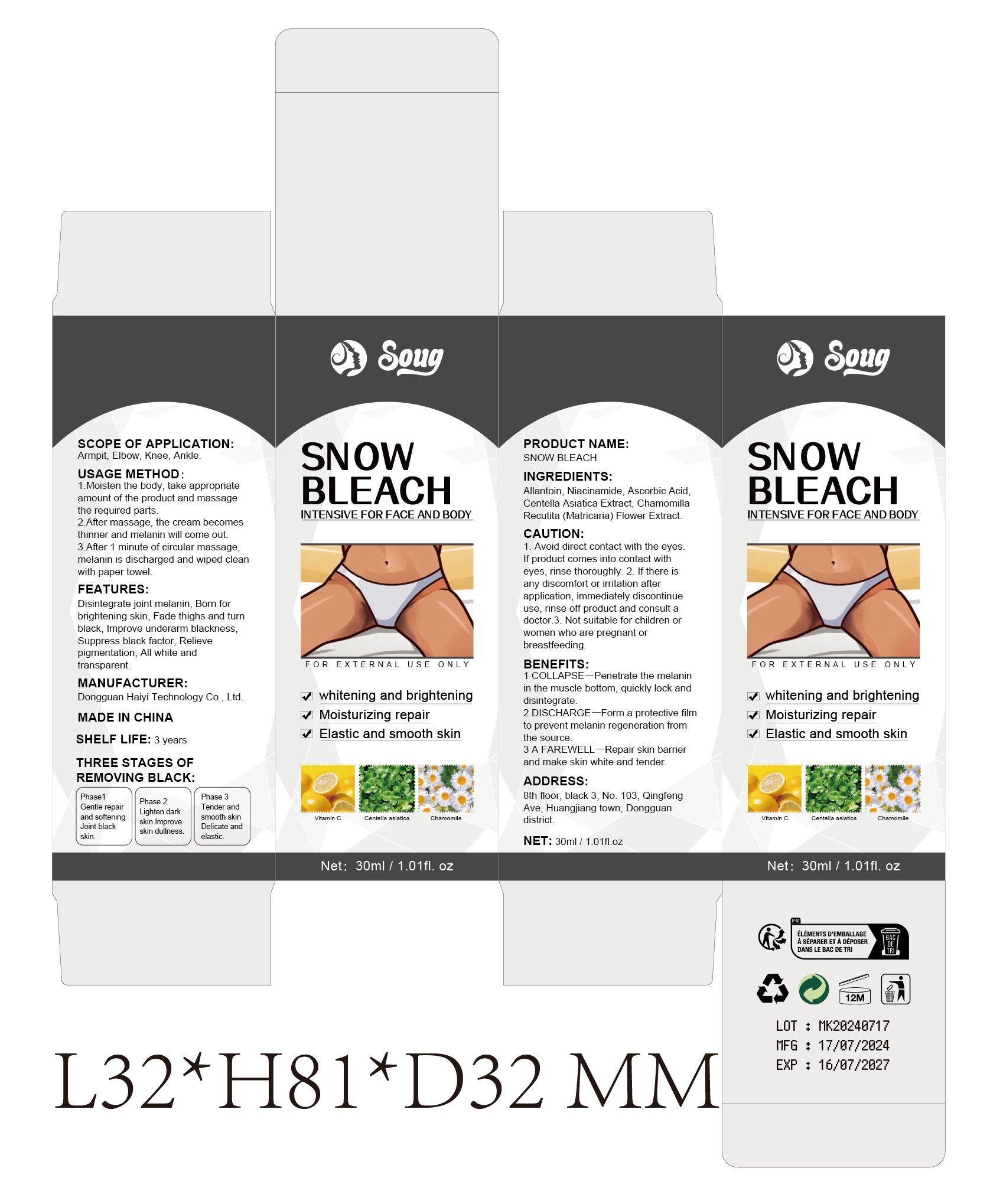 DRUG LABEL: SNOW BLEACH
NDC: 84732-021 | Form: CREAM
Manufacturer: Dongguan Haiyi Technology Co.,Ltd.
Category: otc | Type: HUMAN OTC DRUG LABEL
Date: 20240927

ACTIVE INGREDIENTS: ALLANTOIN 1 mg/30 mL
INACTIVE INGREDIENTS: NIACINAMIDE; CENTELLA ASIATICA TRITERPENOIDS; CHAMOMILE; ASCORBIC ACID

Active ingredient

Allantoin

Inactive ingredient

Niacinamide, Ascorbic AcidCentella Asiatica Extract, ChamomillaRecutita (Matricaria) Flower Extract.

Purpose section

1 COLLAPSE-Penetrate the melaninin the muscle bottom, quickly lock anddisintegrate.

2 DISCHARGE-Form a protective filmto prevent melanin regeneration fromthe source.

3 A FAREWELL-Repair skin barrierand make skin white and tender.

Warning

1. Avoid direct contact with the eyes,lf product comes into contact witheyes, rinse thoroughly.

2. lf there isany discomfort or irritation afterapplication, immediately discontinueuse, rinse off product and consult adoctor.

3. Not suitable for children orwomen who are pregnant orbreastfeeding

stop use

This product may cause allergic reactions in asmall number of people.
lf youexperience any discomfort,please stop using it immediately.

not use

Not suitable for use by children, pregnantor breastfeeding people.

OUT OF CHILDREN

KEEP THE PRODUCT OUT OF REACH OF CHILDREN to

HOW TO USE

1.Moisten the body, take appropriateamount of the product and massagethe required parts,

2.After massage, the cream becomesthinner and melanin will come out.

3.After 1 minute of circular massage,melanin is discharged and wiped cleanwith paper towel.

Dosage

take an appropriateamount,Use 2-3 times a week